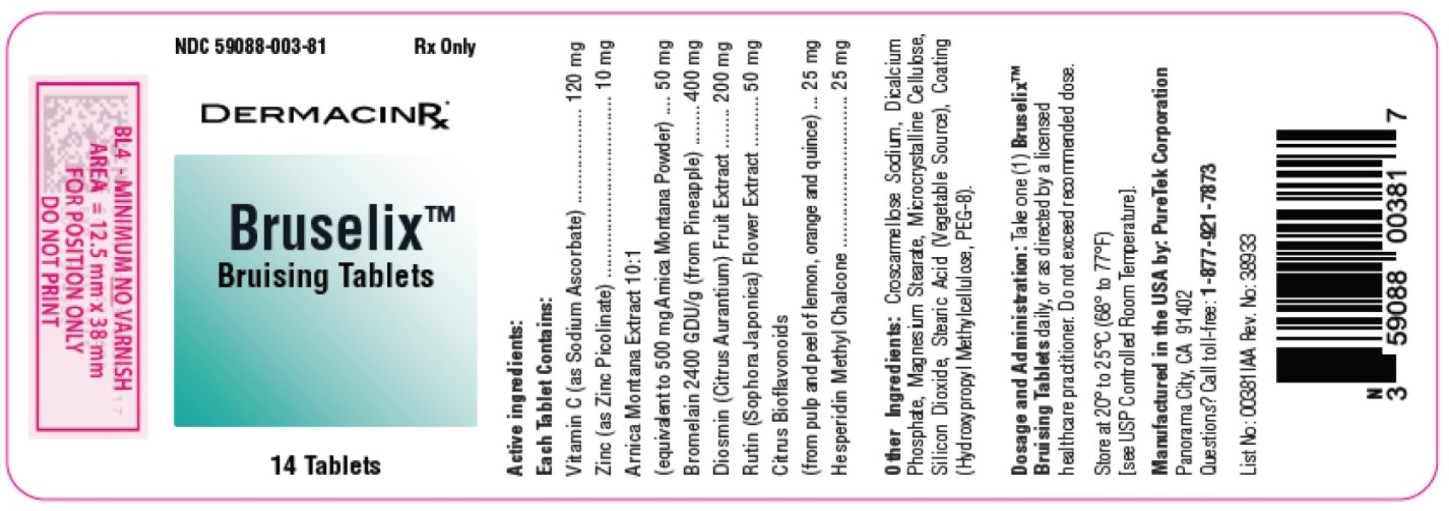 DRUG LABEL: Bruselix Bruising
NDC: 59088-003 | Form: TABLET
Manufacturer: Puretek Corporation
Category: prescription | Type: HUMAN PRESCRIPTION DRUG LABEL
Date: 20241011

ACTIVE INGREDIENTS: ARNICA MONTANA FLOWER 50 mg/1 1; STEM BROMELAIN 400 mg/1 1; SODIUM ASCORBATE 120 mg/1 1; HESPERIDIN METHYLCHALCONE 25 mg/1 1; RUTIN 50 mg/1 1; DIOSMIN 200 mg/1 1; HESPERIDIN 25 mg/1 1; ZINC PICOLINATE 10 mg/1 1
INACTIVE INGREDIENTS: MAGNESIUM STEARATE; STEARIC ACID; POLYETHYLENE GLYCOL 400; MICROCRYSTALLINE CELLULOSE 102; DIBASIC CALCIUM PHOSPHATE DIHYDRATE; SILICON DIOXIDE; HYPROMELLOSE, UNSPECIFIED; CROSCARMELLOSE SODIUM

Bruselix Tablets

DESCRIPTION:

Active Ingredients
Each tablet contains:
Vitamin C (as Sodium Ascorbate) ...............................................................120 mg
Zinc (as Zinc Picolinate) ...............................................................................10 mg
Arnica Montana Extract 10:1 (equivalent to 500 mg Arnica Montana Powder) ...50 mg
Bromelain 2400 GDU/g (from Pineapple) ...................................................400 mg
Diosmin (Citrus Aurantium) Fruit Extract.....................................................200 mg
Rutin (Sophora Japonica) Flower Extract......................................................50 mg
Citrus Bioflavonoids (from pulp and peel of lemon, orange, quince) ............25 mg
Hesperidin Methyl Chalcone..........................................................................25 mg

Other Ingredients: Croscarmellose Sodium, Dicalcium Phosphate, Magnesium Stearate, Microcrystalline Cellulose, Silicon Dioxide, Stearic Acid (Vegetable Source), Coating (Hydroxypropyl Methylcellulose, PEG-8).

INDICATIONS AND USAGE:

Bruselix™ Bruising Tablets are formulated to provide nutritional support during the body’s natural recovery process. They may be helpful for individuals experiencing bruising due to minor injuries, surgical procedures, or sensitive skin. The formula contains antioxidants, enzymes, and natural extracts that are traditionally used to support overall skin health and recovery.

CONTRAINDICATIONS:

Do not use if you have a known allergy to any of the ingredients in Bruselix™ Bruising Tablets, including Arnica Montana or pineapple (Bromelain). Avoid use if you have an allergy to citrus or bioflavonoid components.

WARNINGS AND PRECAUTIONS

Arnica: May cause allergic reactions in sensitive individuals, especially if there is a history of ragweed allergies.

Bromelain: May increase the risk of bleeding in individuals taking anticoagulants or antiplatelet medications. Discontinue use two weeks before surgery.

Zinc and Vitamin C: Use cautiously in individuals with kidney disease or those prone to kidney stones. If you experience an allergic reaction or prolonged bleeding, discontinue use and seek medical attention immediately.

For use on the order of a licensed healthcare practitioner.

Call your doctor about side effects. To report side effects, call PureTek Corporation at 1-877-921-7873.

Drug Interactions:

The use of anticoagulants, such as warfarin or aspirin, may increase the risk of bleeding when combined with Bromelain. High doses of zinc can interfere with the absorption of iron when taken alongside iron supplements. Additionally, citrus bioflavonoids have the potential to enhance the effects of blood pressure-lowering medications.

Adverse Reactions:

Adverse reactions associated with the use of Bruising Tablets may include mild gastrointestinal discomfort, nausea, or allergic reactions such as skin rash. In rare cases, more serious reactions, such as prolonged bleeding or hypersensitivity reactions (e.g., difficulty breathing, swelling), may occur. If you experience any serious adverse effects, discontinue use and seek medical attention immediately.

OVERDOSE:

In the event of overdose, seek medical attention immediately. Symptoms of overdose may include gastrointestinal upset, nausea, or an increased risk of bleeding due to excess Bromelain.

DOSAGE AND ADMINISTRATION:

Take one (1) Bruselix™ Bruising Tablets daily, or as directed by a licensed healthcare practitioner. Do not exceed recommended dose.

HOW SUPPLIED:

Bruselix™ Bruising Tablets are yellow to brown speckled, clear-coated tablets, packaged in a bottle containing 14 tablets – NDC 59088-003-81.

KEEP THIS AND ALL MEDICATIONS OUT OF THE REACH OF CHILDREN. Store at 20°-25°C (68°-77°F) [see USP Controlled Room Temperature]

LABEL

Manufactured by:
PureTek Corporation
Panorama City, CA 91402
For questions or information
call toll-free: 877-921-7873